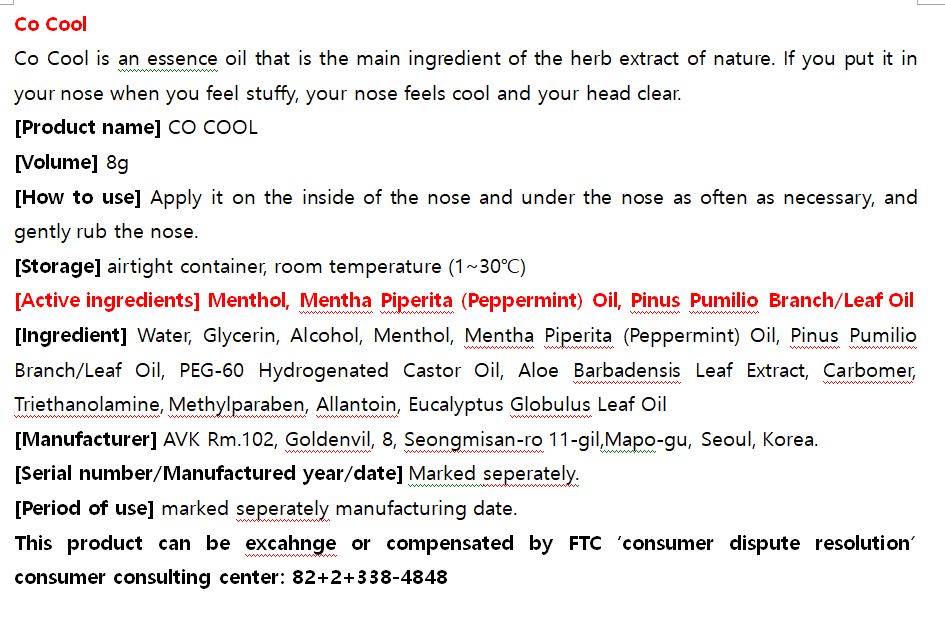 DRUG LABEL: CO COOL
NDC: 72988-0013 | Form: LIQUID
Manufacturer: Lydia Co., Ltd.
Category: otc | Type: HUMAN OTC DRUG LABEL
Date: 20210627

ACTIVE INGREDIENTS: MENTHOL 0.06 g/100 g; PEPPERMINT OIL 0.01 g/100 g; PINE NEEDLE OIL (PINUS MUGO) 0.01 g/100 g
INACTIVE INGREDIENTS: WATER

Drug Facts

ACTIVE INGREDIENT

Menthol, Mentha Piperita (Peppermint) Oil, Pinus Pumilio Branch/Leaf Oil

INACTIVE INGREDIENT

Water, Glycerin, Alcohol, Menthol, Mentha Piperita (Peppermint) Oil, Pinus Pumilio Branch/Leaf Oil, PEG-60 Hydrogenated Castor Oil, Aloe Barbadensis Leaf Extract, Carbomer, Triethanolamine, Methylparaben, Allantoin, Eucalyptus Globulus Leaf Oil

PURPOSE

Co Cool is an essence oil that is the main ingredient of the herb extract of nature. If you put it in your nose when you feel stuffy, your nose feels cool and your head clear.

keep out of reach of the children

INDICATIONS AND USAGE

Apply it on the inside of the nose and under the nose as often as necessary, and gently rub the nose.

WARNINGS

■ don’t use on the part where there is injury, eczema, or dermatitis

■ if swallowed, get medical help or contact a person control center immediately

DOSAGE AND ADMINISTRATION

for nasal use only